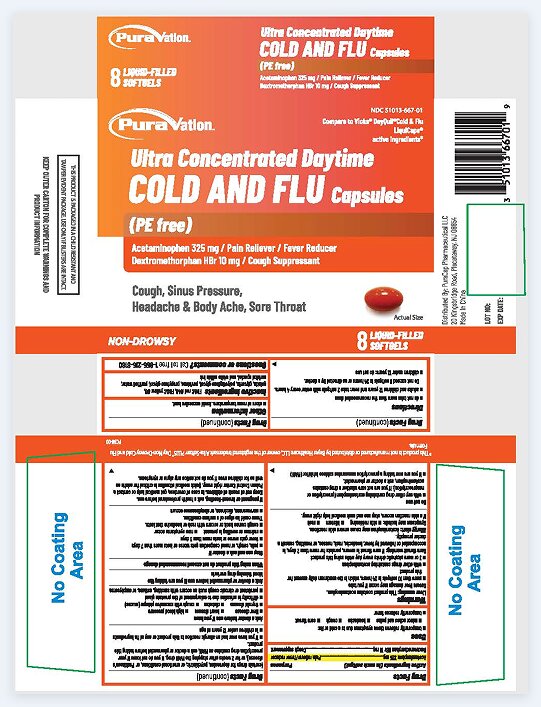 DRUG LABEL: Ultra Concentrated Daytime COLD AND FLU
NDC: 51013-667 | Form: CAPSULE, LIQUID FILLED
Manufacturer: PuraCap Pharmaceutical LLC
Category: otc | Type: HUMAN OTC DRUG LABEL
Date: 20250311

ACTIVE INGREDIENTS: ACETAMINOPHEN 325 mg/1 1; DEXTROMETHORPHAN HYDROBROMIDE 10 mg/1 1
INACTIVE INGREDIENTS: FD&C RED NO. 40; FD&C YELLOW NO. 6; GELATIN; GLYCERIN; POLYETHYLENE GLYCOL, UNSPECIFIED; POVIDONE; PROPYLENE GLYCOL; WATER; SORBITOL

Ultra Concentrated Daytime COLD AND FLU Capsules

Drug Facts

Active ingredients (in each Softgel)

Acetaminophen 325 mg

Dextromethorphan HBr 10 mg

Purpose

Pain reliever/fever reducer

Cough suppressant

Uses

- temporarily relieves these symptoms due to a cold or flu:

- minor aches and pains
- headache
- cough
- sore throat
- temporarily reduces fever

Warnings

Liver warning

This product contains acetaminophen. Severe liver damage may occur if you take

- more than 10 softgels in 24 hours, which is the maximum daily amount for this product
- with other drugs containing acetaminophen
- 3 or more alcoholic drinks every day while using this product

Sore throat warning

If sore throat is severe, persists for more than 2 days, is accompanied or followed by fever, headache, rash, nausea, or vomiting, consult a doctor promptly.

Allergy alert:Acetaminophen may cause severe skin reactions. Symptoms may include:

- skin reddening
- blisters
- rash

If a skin reaction occurs, stop use and seek medical help right away.

Do not use

- with any other drug containing acetaminophen (prescription or nonprescription). If you are not sure whether a drug contains acetaminophen, ask a doctor or pharmacist.
- if you are now taking a prescription monoamine oxidase inhibitor (MAOI) (certain drugs for depression, psychiatric, or emotional conditions, or Parkinson's disease), or for 2 weeks after stopping the MAOI drug. If you do not know if your prescription drug contains an MAOI, ask a doctor or pharmacist before taking this product.
- if you have ever had an allergic reaction to this product or any of its ingredients
- in children under 12 years of age

Ask a doctor before use if you have

- liver disease
- heart disease
- high blood pressure
- thyroid disease
- diabetes
- cough with excessive phlegm (mucus)
- difficulty in urination due to enlargement of the prostate gland
- persistent or chronic cough such as occurs with smoking, asthma, or emphysema

Ask a doctor or pharmacist before use if you are taking the blood thinning drug warfarin

When using this product do not exceed recommended dosage

Stop use and ask a doctor if

- pain, cough gets worse or lasts more than 7 days
- fever gets worse or lasts more than 3 days
- redness or swelling is present
- new symptoms occur
- cough comes back or occurs with rash or headache that lasts.
  These could be signs of a serious condition.
- nervousness, dizziness, or sleeplessness occurs

PREGNANCY OR BREAST FEEDING

If pregnant or breast-feeding, ask a health professional before use.

Keep out of reach of children. In case of overdose, get medical help or contact a Poison Control Center right away. Quick medical attention is critical for adults as well as for children even if you do not notice any signs or symptoms.

Directions

- do not take more than the recommended dose
- adults and children 12 years and over: take 2 softgels with water every 4 hours. Do not exceed 8 softgels in 24 hours or as directed by a doctor
- children under 12 years: do not use

Other information

- Store at room temperature. Avoid excessive heat.

Inactive ingredients

FD&C red #40, FD&C yellow #6, gelatin, glycerin, polyethylene glycol, povidone, propylene glycol, purified water, sorbitol special, white edible ink

Questions or comments?

Call toll free: 1-855-215-8180

PRINCIPAL DISPLAY PANEL

Ultra Concentrated Daytime COLD AND FLU Capsules 8 SOFTGELS

NDC 51013-667-01

*Compare to the active ingredients in Vicks®DayQuil® Cold&Flu LiquiCaps®